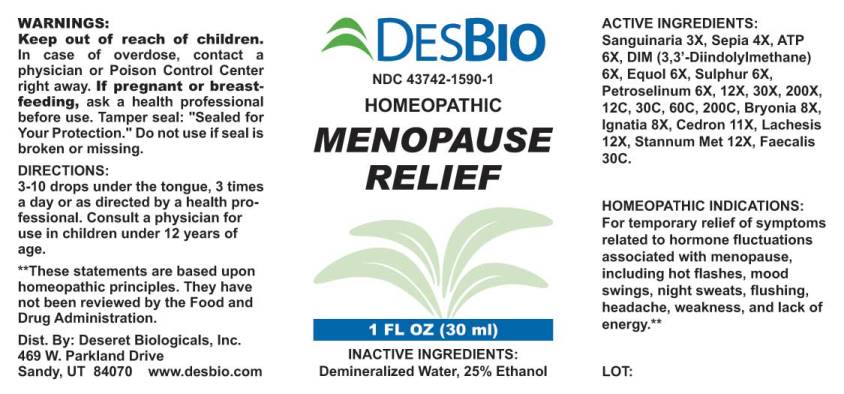 DRUG LABEL: Menopause Relief
NDC: 43742-1590 | Form: LIQUID
Manufacturer: Deseret Biologicals, Inc.
Category: homeopathic | Type: HUMAN OTC DRUG LABEL
Date: 20240814

ACTIVE INGREDIENTS: SANGUINARIA CANADENSIS ROOT 3 [hp_X]/1 mL; SEPIA OFFICINALIS JUICE 4 [hp_X]/1 mL; ADENOSINE TRIPHOSPHATE DISODIUM 6 [hp_X]/1 mL; 3,3'-DIINDOLYLMETHANE 6 [hp_X]/1 mL; EQUOL, (-)- 6 [hp_X]/1 mL; SULFUR 6 [hp_X]/1 mL; PETROSELINUM CRISPUM 6 [hp_X]/1 mL; BRYONIA ALBA ROOT 8 [hp_X]/1 mL; STRYCHNOS IGNATII SEED 8 [hp_X]/1 mL; SIMABA CEDRON SEED 11 [hp_X]/1 mL; LACHESIS MUTA VENOM 12 [hp_X]/1 mL; TIN 12 [hp_X]/1 mL; ALCALIGENES FAECALIS 30 [hp_C]/1 mL
INACTIVE INGREDIENTS: WATER; ALCOHOL

Drug Facts:

ACTIVE INGREDIENTS:

Sanguinaria Canadensis 3X, Sepia 4X, Adenosinum Triphosphoricum Dinatrum 6X, DIM (3,3’-Diindolymethane) 6X, Equol 6X, Sulphur 6X, Petroselinum Sativum 6X, 12X, 30X, 200X, 12C, 30C, 60C, 200C, Bryonia (Alba) 8X, Ignatia Amara 8X, Cedron 11X, Lachesis Mutus 12X, Stannum Metallicum 12X, Faecalis (Alkaligenes) 30C.

HOMEOPATHIC INDICATIONS:

For temporary relief of symptoms related to hormone fluctuations associated with menopause, including hot flashes, mood swings, night sweats, flushing, headache, weakness, and lack of energy.**
**These statements are based upon homeopathic principles. They have not been reviewed by the Food and Drug Administration.

WARNINGS:

Keep out of reach of children. In case of overdose, contact a physician or Poison Control Center right away.
If pregnant or breast-feeding, ask a health professional before use.
Tamper seal: "Sealed for Your Protection." Do not use if seal is broken or missing.

Keep out of reach of children. In case of overdose, contact a physician or Poison Control Center right away.

DIRECTIONS:

3-10 drops under the tongue, 3 times a day or as directed by a health professional. Consult a physician for use in children under 12 years of age.

HOMEOPATHIC INDICATIONS:

For temporary relief of symptoms related to hormone fluctuations associated with menopause, including hot flashes, mood swings, night sweats, flushing, headache, weakness, and lack of energy.**
**These statements are based upon homeopathic principles. They have not been reviewed by the Food and Drug Administration.

INACTIVE INGREDIENTS:

Demineralized Water, 25% Ethanol

QUESTIONS:

Dist. By: Deseret Biologicals, Inc.
469 W. Parkland Drive
Sandy, UT 84070 www.desbio.com

PACKAGE LABEL DISPLAY:

DESBIO
NDC 43742-1590-1
HOMEOPATHIC
MENOPAUSE
RELIEF
1 FL OZ (30 ml)